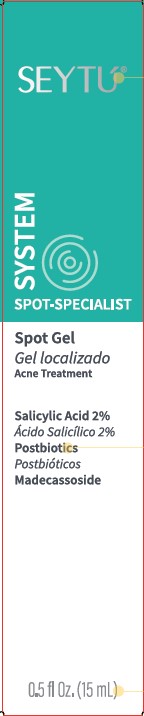 DRUG LABEL: SEYTU Spot
NDC: 84271-002 | Form: GEL
Manufacturer: Omnilife USA, Inc.
Category: otc | Type: HUMAN OTC DRUG LABEL
Date: 20240823

ACTIVE INGREDIENTS: SALICYLIC ACID 2 g/100 mL
INACTIVE INGREDIENTS: ALCOHOL; ALLANTOIN; AMMONIUM POLYACRYLOYLDIMETHYL TAURATE (55000 MPA.S); BUTYLENE GLYCOL; ETHYLHEXYLGLYCERIN; MADECASSOSIDE; PHENOXYETHANOL; PURSLANE; PROPYLENE GLYCOL; SODIUM HYDROXIDE; EDETATE SODIUM; WATER

SEYTÚ® Spot Gel

Active Ingredient

Salicylic Acid 2.0%

Purpose

Acne Treatment Gel

Uses

- For the treatment of acne
- Reduce the severity of new acne pimples, blackheads, or whiteheads

Warnings

- For external use only
- If experience skin irritation or prolonged stinging, stop using the product and consult your physician

When using this product

- skin irritation and dryness is more likely to occur if you use another topical acne medication at the same time. If irritation occurs, only use one topical acne medication at a time
- Follow the use instructions on the label
- Do not exceed the recommended applications

Keep out of reach of children.

- If swallowed, get medical help or contact a poison control center right away. Avoid contact with eyes. If contact occurs, flush thoroughly with water.

Directions

- Clean the skin thoroughly before applying this product
- Cover the entire affected area with a thin layer one to three times daily
- Because excessive drying of the skin may occur, start with one application daily, then gradually increase to two or three times daily if needed or as directed by a doctor
- If bothersome dryness or peeling occurs, reduce application to once a day or every other day

Other Information

Do not use if the security seal has been broken

Inactive Ingredients

Alcohol Denat., Allantoin, Ammonium Polyacryloyldimethyl Taurate, Bacillus Ferment Filtrate Extract, Butylene Glycol, Ethylhexylglycerin, Madecassoside, Phenoxyethanol, Portulaca Oleracea Extract, Propylene Glycol, Sodium Hydroxide, Tetrasodium EDTA, Water (Aqua).

Questions?

CUSTOMER SERVICE: U.S.A. 1 844 847 3988.
seytu.omnilife.com

Principal Display Panel

SEYTÚ®
SYSTEM
SPOT-SPECIALIST
Spot Gel
Gel Localizado
Acne Treatment
Salicylic Acid 2%
Ácido Salicílico 2%
Postbiotics
Postbióticos
Madecassoside
0.5 fl Oz. (15 mL)
MADE IN USA WITH
GLOBALLY SOURCED
INGREDIENTS
PRODUCT NOT TESTED
ON ANIMALS

HYPOALLERGENIC
PRODUCT
IMPORTED AND / OR DISTRIBUTED BY:
OMNILIFE USA, INC. 3900 SOUTH
FREEWAY, FORT WORTH, TX 76110.

Label